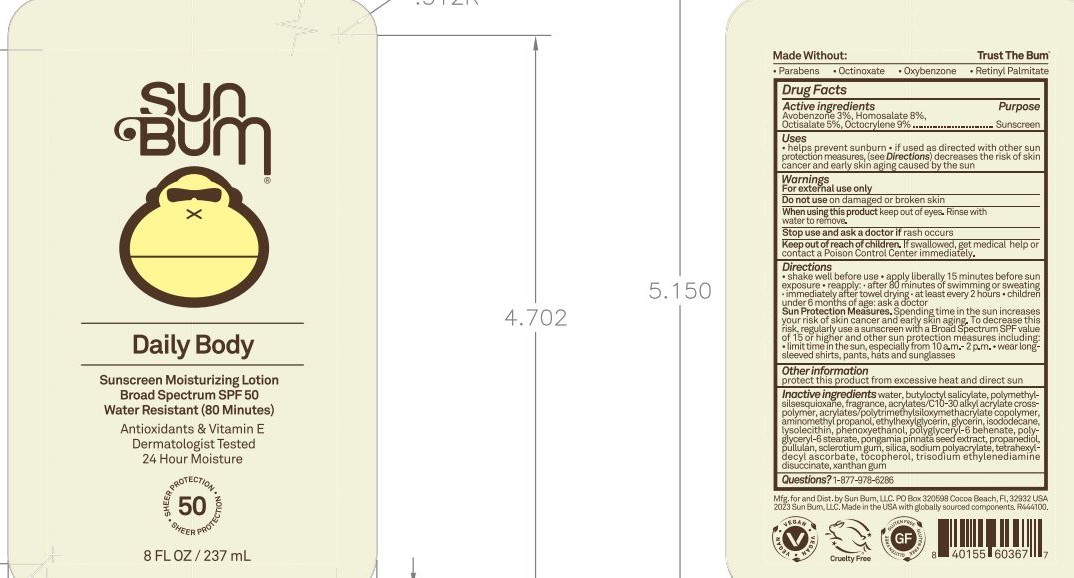 DRUG LABEL: Sun Bum Daily Body
NDC: 69039-663 | Form: LOTION
Manufacturer: Sun Bum, LLC
Category: otc | Type: HUMAN OTC DRUG LABEL
Date: 20250923

ACTIVE INGREDIENTS: OCTISALATE 50 mg/1 mL; AVOBENZONE 30 mg/1 mL; OCTOCRYLENE 90 mg/1 mL; HOMOSALATE 80 mg/1 mL
INACTIVE INGREDIENTS: PROPANEDIOL; PHENOXYETHANOL; ISODODECANE; POLYGLYCERYL-6 BEHENATE; GLYCERIN; POLYMETHYLSILSESQUIOXANE (11 MICRONS); FRAGRANCE 13576; BUTYLOCTYL SALICYLATE; AMINOMETHYL PROPANOL; LYSOPHOSPHATIDYLCHOLINE, SOYBEAN; TOCOPHEROL; TETRAHEXYLDECYL ASCORBATE; SODIUM POLYACRYLATE (2500000 MW); ETHYLHEXYLGLYCERIN; TRISODIUM ETHYLENEDIAMINE DISUCCINATE; PULLULAN; POLYGLYCERYL-6 STEARATE; WATER; BUTYL ACRYLATE/METHYL METHACRYLATE/TRIMETHYLSILOXYMETHACRYLATE COPOLYMER; PONGAMIA PINNATA SEED; XANTHAN GUM; ACRYLATES/C10-30 ALKYL ACRYLATE CROSSPOLYMER (60000 MPA.S); SCLEROTIUM GUM; SILICA

Sun Bum Daily Body

Active ingredients

Avobenzone 3%, Homosalate 8%, Octisalate 5%, Octocrylene 9%

Purpose

Sunscreen

Uses

• helps prevent sunburn

• if used as directed with other sun protection measures, (see Directions) decreases the risk of skin cancer and early skin aging caused by the sun

Warnings

For external use only

Do not use on damaged or broken skin

When using this product keep out of eyes. Rinse with water to remove.

Stop use and ask a doctor if rash occurs

Keep out of reach of children. If swallowed, get medical help or contact a Poison Control Center immediately.

Warnings

Keep Out Of Reach Of Children

Directions

• shake well before use

• apply liberally 15 minutes before sun exposure

• reapply: • after 80 minutes of swimming or sweating • immediately after towel drying • at least every 2 hours

• children under 6 months of age: ask a doctor

• Sun Protection Measures. Spending time in the sun increases your risk of skin cancer and early skin aging. To decrease this risk, regularly use a sunscreen with a Broad Spectrum SPF value of 15 or higher and other sun protection measures including:

• limit time in the sun, especially from 10 a.m.- 2 p.m.

• wear long-sleeved shirts, pants, hats and sunglasses

Directions

• shake well before use

• apply liberally 15 minutes before sun exposure

Other information

protect this product from excessive heat and direct sun

Inactive ingredients

water, butyloctyl salicylate, polymethyl-silsesquioxane, fragrance, acrylates/C10-30 alkyl acrylate cross-polymer, acrylates/polytrimethylsiloxymethacrylate copolymer, aminomethyl propanol, ethylhexylglycerin, glycerin, isododecane, lysolecithin, phenoxyethanol, polyglyceryl-6 behenate, polyglyceryl-6 stearate, pongamia pinnata seed extract, propanediol, pullulan, sclerotium gum, silica, sodium polyacrylate, tetrahexyldecyl ascorbate, tocopherol, trisodium ethylenediamine disuccinate, xanthan gum

Questions?

1-877-978-6286